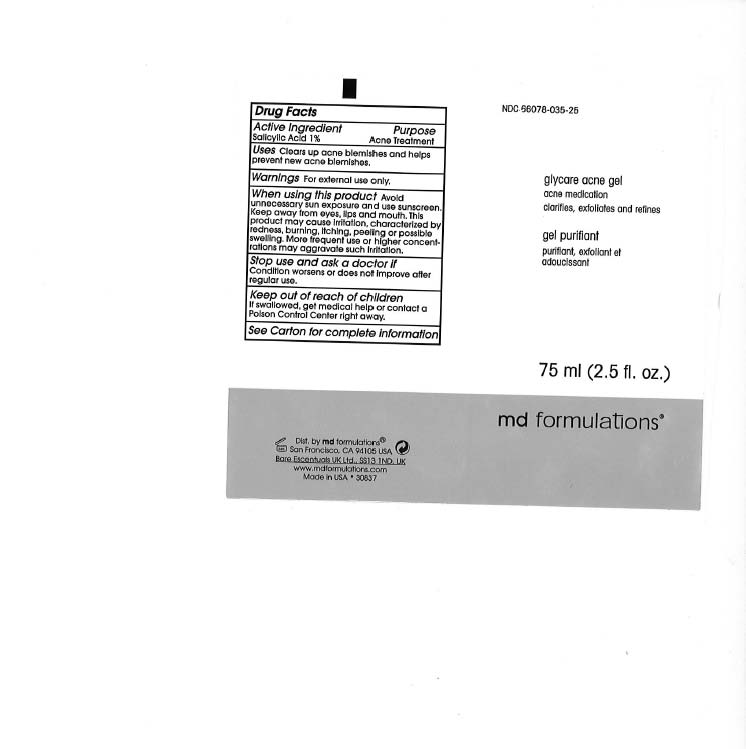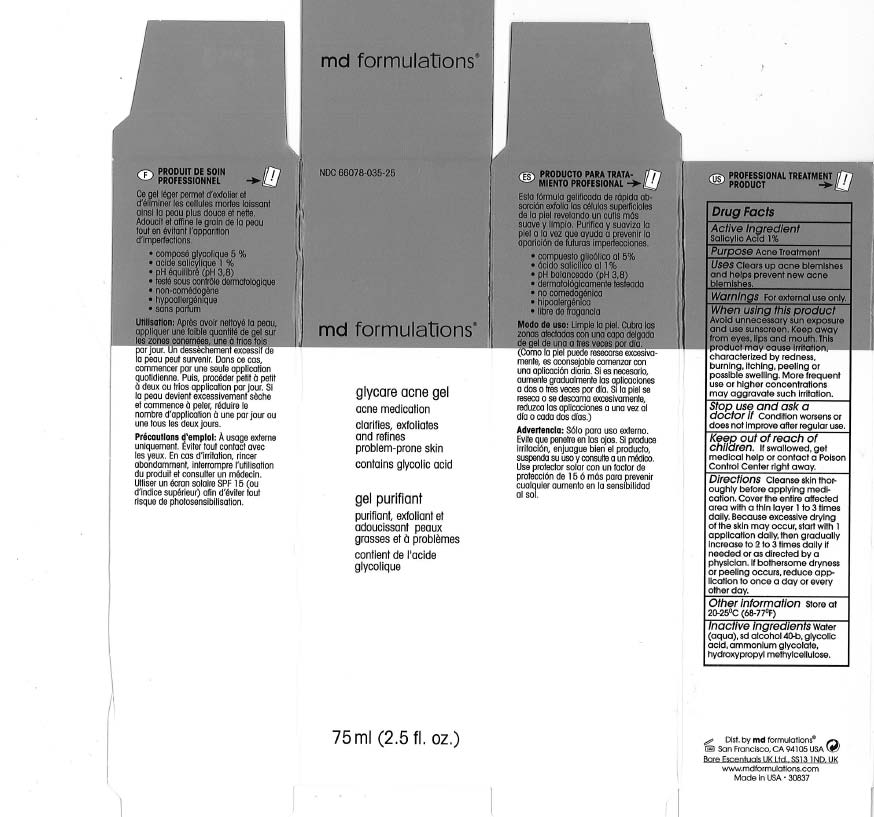 DRUG LABEL: Glycare Acne
NDC: 66078-035 | Form: GEL
Manufacturer: MD Formulation
Category: otc | Type: HUMAN OTC DRUG LABEL
Date: 20110705

ACTIVE INGREDIENTS: SALICYLIC ACID 1 g/100 g
INACTIVE INGREDIENTS: WATER; GLYCOLIC ACID; HYPROMELLOSE 2208 (15000 MPA.S)

Glycare Acne Gel

ACTIVE INGREDIENT

Salicylic Acid 1%

PURPOSE

Acne Tratment

KEEP OUT OF REACH OF CHILDREN

If swallowed, get medical help or contact a Poison Control Center right away.

INDICATIONS AND USAGE

Clears up acne blemishes and helps prevent new acne blemishes.

WARNINGS

For external use only.

DOSAGE AND ADMINISTRATION

Directions Cleanse skin thoroughly before applying medication.Cover the entire affected area with a thin layer 1 to 3 times dally. Because excessive drying of the skin may occur, start with 1 application daily, then gradually increase to 2 to 3 times daily if needed or as directed by a physician. If bothersome dryness or peeling occurs, reduce application to once a day or every other day.

INACTIVE INGREDIENT

Water (aqua), sd alcohol 40-b, glycolic acid, ammonium glycolate, hydroxypropyl melhylcellulose.